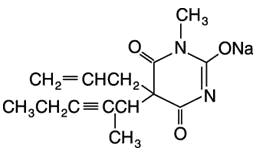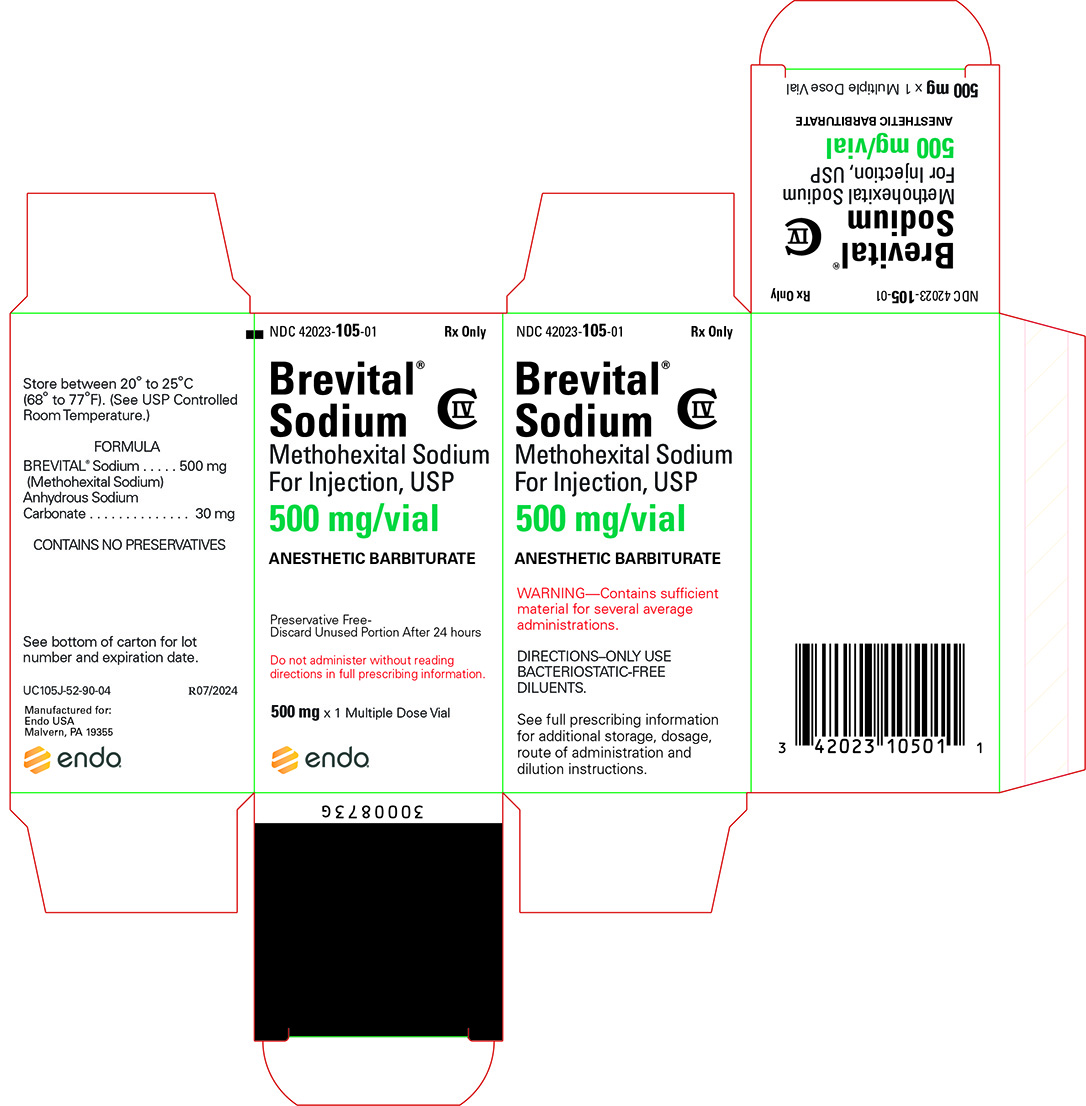 DRUG LABEL: Brevital Sodium
NDC: 42023-105 | Form: INJECTION, POWDER, LYOPHILIZED, FOR SOLUTION
Manufacturer: Par Health USA, LLC
Category: prescription | Type: HUMAN PRESCRIPTION DRUG LABEL
Date: 20240807
DEA Schedule: CIV

ACTIVE INGREDIENTS: METHOHEXITAL SODIUM 500 mg/1 1
INACTIVE INGREDIENTS: SODIUM HYDROXIDE; SODIUM CARBONATE

BREVITAL®
(methohexital sodium) for injection, USP

CIV

For Intravenous Use in Adults

For Rectal and Intramuscular Use Only in Pediatric Patients

WARNING

BREVITAL should be used only in hospital or ambulatory care settings that provide for continuous monitoring of respiratory (e.g. pulse oximetry) and cardiac function. Immediate availability of resuscitative drugs and age- and size-appropriate equipment for bag/valve/mask ventilation and intubation and personnel trained in their use and skilled in airway management should be assured. For deeply sedated patients, a designated individual other than the practitioner performing the procedure should be present to continuously monitor the patient. (See WARNINGS.)

DESCRIPTION

BREVITAL® (methohexital sodium, USP) for injection, is 2,4,6 (1H, 3H, 5H)-Pyrimidinetrione, 1-methyl-5-(1-methyl-2-pentynyl)-5-(2-propenyl)-, (±)-, monosodium salt and has the empirical formula C14H17N2NaO3. Its molecular weight is 284.29.

The structural formula is as follows:

Methohexital sodium is a rapid, ultrashort-acting barbiturate anesthetic. Methohexital sodium for injection is a freeze-dried, sterile, nonpyrogenic mixture of methohexital sodium with 6% anhydrous sodium carbonate added as a buffer. It contains not less than 90% and not more than 110% of the labeled amount of methohexital sodium. It occurs as a white, freeze-dried plug that is freely soluble in water.

This product is oxygen sensitive. The pH of the 1% solution is between 10 and 11; the pH of the 0.2% solution in 5% dextrose is between 9.5 and 10.5.

Methohexital sodium may be administered by direct intravenous injection or continuous intravenous drip, intramuscular or rectal routes (see PRECAUTIONS/Pediatric Use). Reconstituting instructions vary depending on the route of administration (see DOSAGE AND ADMINISTRATION).

CLINICAL PHARMACOLOGY

Compared with thiamylal and thiopental, methohexital is at least twice as potent on a weight basis, and its duration of action is only about half as long. Although the metabolic fate of methohexital in the body is not clear, the drug does not appear to concentrate in fat depots to the extent that other barbiturate anesthetics do. Thus, cumulative effects are fewer and recovery is more rapid with methohexital than with thiobarbiturates. In experimental animals, the drug cannot be detected in the blood 24 hours after administration.

Methohexital differs chemically from the established barbiturate anesthetics in that it contains no sulfur. Little analgesia is conferred by barbiturates; their use in the presence of pain may result in excitation.

Intravenous administration of methohexital results in rapid uptake by the brain (within 30 seconds) and rapid induction of sleep.

Following intramuscular administration to pediatric patients, the onset of sleep occurs in 2 to 10 minutes. A plasma concentration of 3 mcg/mL was achieved in pediatric patients 15 minutes after an intramuscular dose (10 mg/kg) of a 5% solution. Following rectal administration to pediatric patients, the onset of sleep occurs in 5 to 15 minutes. Plasma methohexital concentrations achieved following rectal administration tend to increase both with dose and with the use of more dilute solution concentrations when using the same dose. A 25 mg/kg dose of a 1% methohexital solution yielded plasma concentrations of 6.9 to 7.9 mcg/mL 15 minutes after dosing. The absolute bioavailability of rectal methohexital sodium is 17%.

With single doses, the rate of redistribution determines duration of pharmacologic effect. Metabolism occurs in the liver through demethylation and oxidation. Side-chain oxidation is the most important biotransformation involved in termination of biologic activity. Excretion occurs via the kidneys through glomerular filtration.

INDICATIONS AND USAGE

BREVITAL can be used in adults as follows:

1. For intravenous induction of anesthesia prior to the use of other general anesthetic agents.

2. For intravenous induction of anesthesia and as an adjunct to subpotent inhalational anesthetic agents (such as nitrous oxide in oxygen) for short surgical procedures; BREVITAL may be given by infusion or intermittent injection.

3. For use along with other parenteral agents, usually narcotic analgesics, to supplement subpotent inhalational anesthetic agents (such as nitrous oxide in oxygen) for longer surgical procedures.

4. As intravenous anesthesia for short surgical, diagnostic, or therapeutic procedures associated with minimal painful stimuli (see WARNINGS).

5. As an agent for inducing a hypnotic state.

BREVITAL can be used in pediatric patients older than 1 month as follows:

1. For rectal or intramuscular induction of anesthesia prior to the use of other general anesthetic agents.

2. For rectal or intramuscular induction of anesthesia and as an adjunct to subpotent inhalational anesthetic agents for short surgical procedures.

3. As rectal or intramuscular anesthesia for short surgical, diagnostic, or therapeutic procedures associated with minimal painful stimuli.

CONTRAINDICATIONS

BREVITAL is contraindicated in patients in whom general anesthesia is contraindicated, in those with latent or manifest porphyria, or in patients with a known hypersensitivity to barbiturates.

WARNINGS

As with all potent anesthetic agents and adjuncts, BREVITAL should be used only in hospital or ambulatory care settings that provide for continuous monitoring of respiratory (e.g. pulse oximetry) and cardiac function. Immediate availability of resuscitative drugs and age- and size-appropriate equipment for bag/valve/mask ventilation and intubation and personnel trained in their use and skilled in airway management should be assured. For deeply sedated patients, a designated individual other than the practitioner performing the procedure should be present to continuously monitor the patient.

Maintenance of a patent airway and adequacy of ventilation must be ensured during induction and maintenance of anesthesia with methohexital sodium solution. Laryngospasm is common during induction with all barbiturates and may be due to a combination of secretions and accentuated reflexes following induction or may result from painful stimuli during light anesthesia. Apnea/hypoventilation may be noted during induction, which may impair pulmonary ventilation; the duration of apnea may be longer than that produced by other barbiturate anesthetics. Cardiorespiratory arrest may occur.

This prescribing information describes intravenous use of methohexital sodium in adults. It also discusses intramuscular and rectal administration in pediatric patients older than one month. Although the published literature discusses intravenous administration in pediatric patients, the safety and effectiveness of intravenous administration of methohexital sodium in pediatric patients have not been established in well-controlled, prospective studies. (See PRECAUTIONS/Pediatric Use.)

Seizures may be elicited in subjects with a previous history of convulsive activity, especially partial seizure disorders.

Because the liver is involved in demethylation and oxidation of methohexital and because barbiturates may enhance preexisting circulatory depression, severe hepatic dysfunction, severe cardiovascular instability, or a shock-like condition may be reason for selecting another induction agent.

Prolonged administration may result in cumulative effects, including extended somnolence, protracted unconsciousness, and respiratory and cardiovascular depression. Respiratory depression in the presence of an impaired airway may lead to hypoxia, cardiac arrest, and death.

The CNS-depressant effect of BREVITAL may be additive with that of other CNS depressants, including ethyl alcohol and propylene glycol.

DANGER OF INTRA-ARTERIAL INJECTION—Unintended intra-arterial injection of barbiturate solutions may be followed by the production of platelet aggregates and thrombosis, starting in arterioles distal to the site of injection. The resulting necrosis may lead to gangrene, which may require amputation. The first sign in conscious patients may be a complaint of fiery burning that roughly follows the distribution path of the injected artery; if noted, the injection should be stopped immediately and the situation reevaluated. Transient blanching may or may not be noted very early; blotchy cyanosis and dark discoloration may then be the first sign in anesthetized patients. There is no established treatment other than prevention. The following should be considered prior to injection:

1. The extent of injury is related to concentration. Concentrations of 1% methohexital will usually suffice; higher concentrations should ordinarily be avoided.

2. Check the infusion to ensure that the catheter is in the lumen of a vein before injection.

Injection through a running intravenous infusion may enhance the possibility of detecting arterial placement; however, it should be remembered that the characteristic bright-red color of arterial blood is often altered by contact with drugs. The possibility of aberrant arteries should always be considered.

Post injury arterial injection of vasodilators and/or arterial infusion of parenteral fluids are generally regarded to be of no value in altering outcome. Animal experiments and published individual case reports concerned with a variety of arteriolar irritants, including barbiturates, suggest that 1 or more of the following may be of benefit in reducing the area of necrosis:

1. Arterial injection of heparin at the site of injury, followed by systemic anticoagulation.

2. Sympathetic blockade (or brachial plexus blockade in the arm).

3. Intra-arterial glucocorticoid injection at the site of injury, followed by systemic steroids.

4. A case report (nonbarbiturate injury) suggests that intra-arterial urokinase may promote fibrinolysis, even if administered late in treatment.

If extravasation is noted during injection of methohexital, the injection should be discontinued until the situation is remedied. Local irritation may result from extravasation; subcutaneous swelling may also serve as a sign of arterial or periarterial placement of the catheter.

Pediatric Neurotoxicity

Published animal studies demonstrate that the administration of anesthetic and sedation drugs that block NMDA receptors and/or potentiate GABA activity increase neuronal apoptosis in the developing brain and result in long-term cognitive deficits when used for longer than 3 hours. The clinical significance of these findings is not clear. However, based on the available data, the window of vulnerability to these changes is believed to correlate with exposures in the third trimester of gestation through the first several months of life, but may extend out to approximately three years of age in humans. (See PRECAUTIONS/Pregnancy, Pediatric Use, and ANIMAL TOXICOLOGY AND/OR PHARMACOLOGY).

Some published studies in children suggest that similar deficits may occur after repeated or prolonged exposures to anesthetic agents early in life and may result in adverse cognitive or behavioral effects. These studies have substantial limitations, and it is not clear if the observed effects are due to the anesthetic/sedation drug administration or other factors such as the surgery or underlying illness.

Anesthetic and sedation drugs are a necessary part of the care of children needing surgery, other procedures, or tests that cannot be delayed, and no specific medications have been shown to be safer than any other. Decisions regarding the timing of any elective procedures requiring anesthesia should take into consideration the benefits of the procedure weighed against the potential risks.

PRECAUTIONS

General

All routes of administration of BREVITAL are often associated with hiccups, coughing, and/or muscle twitching, which may also impair pulmonary ventilation. Following induction, temporary hypotension and tachycardia may occur.

Recovery from methohexital anesthesia is rapid and smooth. The incidence of postoperative nausea and vomiting is low if the drug is administered to fasting patients. Postanesthetic shivering has occurred in a few instances.

The usual precautions taken with any barbiturate anesthetic should be observed with BREVITAL. The drug should be used with caution in patients with asthma, obstructive pulmonary disease, severe hypertension or hypotension, myocardial disease, congestive heart failure, severe anemia, or extreme obesity.

Methohexital sodium should be used with extreme caution in patients in status asthmaticus. Caution should be exercised in debilitated patients or in those with impaired function of respiratory, circulatory, renal, hepatic, or endocrine systems.

Information for Patients

Risk of Drowsiness

When appropriate, patients should be instructed as to the hazards of drowsiness that may follow use of BREVITAL. Outpatients should be released in the company of another individual, and no skilled activities, such as operating machinery or driving a motor vehicle, should be engaged in for 8 to 12 hours.

Effect of anesthetic and sedation drugs on early brain development

Studies conducted in young animals and children suggest repeated or prolonged use of general anesthetic or sedation drugs in children younger than 3 years may have negative effects on their developing brains. Discuss with parents and caregivers the benefits, risks, and timing and duration of surgery or procedures requiring anesthetic and sedation drugs (See WARNINGS/Pediatric Neurotoxicity).

Laboratory Tests

BSP and liver function studies may be influenced by administration of a single dose of barbiturates.

Drug Interactions

Prior chronic administration of barbiturates or phenytoin (e.g. for seizure disorder) appears to reduce the effectiveness of BREVITAL. Barbiturates may influence the metabolism of other concomitantly used drugs, such as phenytoin, halothane, anticoagulants, corticosteroids, ethyl alcohol, and propylene glycol-containing solutions.

Carcinogenesis, Mutagenesis, Impairment of Fertility

Carcinogenesis

Long-term animal studies to evaluate the carcinogenic potential of methohexital have not been conducted.

Mutagenesis

Methohexital was negative in the in vitro bacterial reverse mutation assay (Ames test) using Salmonella typhimurium strains TA97, TA98, TA100, and TA1535.

Impairment of Fertility

Reproduction studies in animals have revealed no evidence of impaired fertility.

Pregnancy

Risk Summary

There are no adequate and well-controlled studies in pregnant women. In animal reproduction studies, no adverse developmental effects were observed following administration of methohexital to pregnant rabbits and rats during organogenesis at doses up to 4 and 7 times the human dose respectively.

Published studies in pregnant primates demonstrate that the administration of anesthetic and sedation drugs that block NMDA receptors and/or potentiate GABA activity during the period of peak brain development increases neuronal apoptosis in the developing brain of the offspring when used for longer than 3 hours. There are no data on pregnancy exposures in primates corresponding to periods prior to the third trimester in humans [See Data].

The estimated background risk of major birth defects and miscarriage for the indicated population is unknown. All pregnancies have a background risk of birth defect, loss, or other adverse outcomes. In the U.S. general population, the estimated background risk of major birth defects and miscarriage in clinically recognized pregnancies is 2-4% and 15-20%, respectively.

Data

Animal Data

Reproduction studies have been performed in rabbits and rats at doses up to 4 and 7 times the human dose respectively and have revealed no evidence of harm to the fetus due to methohexital sodium.

In a published study in primates, administration of an anesthetic dose of ketamine for 24 hours on Gestation Day 122 increased neuronal apoptosis in the developing brain of the fetus. In other published studies, administration of either isoflurane or propofol for 5 hours on Gestation Day 120 resulted in increased neuronal and oligodendrocyte apoptosis in the developing brain of the offspring. With respect to brain development, this time period corresponds to the third trimester of gestation in the human. The clinical significance of these findings is not clear; however, studies in juvenile animals suggest neuroapoptosis correlates with long-term cognitive deficits. (See WARNINGS/Pediatric Neurotoxicity, PRECAUTIONS/Pediatric Use, and ANIMAL TOXICOLOGY AND/OR PHARMACOLOGY).

Labor and Delivery

BREVITAL has been used in cesarean section delivery but, because of its solubility and lack of protein binding, it readily and rapidly traverses the placenta.

Nursing Mothers

Caution should be exercised when BREVITAL is administered to a nursing woman.

Pediatric Use

The safety and effectiveness of methohexital sodium in pediatric patients below the age of 1 month have not been established. Seizures may be elicited in subjects with a previous history of convulsive activity, especially partial seizure disorders. Apnea has been reported following dosing with methohexital regardless of the route of administration used. Studies using methohexital sodium intravenously in pediatric patients have been reported in the published literature. This literature is not adequate to establish the safety and effectiveness of intravenous administration of methohexital sodium in pediatric patients. Due to a variety of limitations such as study design, biopharmaceutic issues, and the wide range of effects observed with similar doses of intravenous methohexital, additional studies of intravenous methohexital in pediatric patients are necessary before this route can be recommended in pediatric patients. (See WARNINGS)

Published juvenile animal studies demonstrate that the administration of anesthetic and sedation drugs, such as BREVITAL, that either block NMDA receptors or potentiate the activity of GABA during the period of rapid brain growth or synaptogenesis, results in widespread neuronal and oligodendrocyte cell loss in the developing brain and alterations in synaptic morphology and neurogenesis. Based on comparisons across species, the window of vulnerability to these changes is believed to correlate with exposures in the third trimester of gestation through the first several months of life, but may extend out to approximately 3 years of age in humans.

In primates, exposure to 3 hours of ketamine that produced a light surgical plane of anesthesia did not increase neuronal cell loss, however, treatment regimens of 5 hours or longer of isoflurane increased neuronal cell loss. Data from isoflurane-treated rodents and ketamine-treated primates suggest that the neuronal and oligodendrocyte cell losses are associated with prolonged cognitive deficits in learning and memory. The clinical significance of these nonclinical findings is not known, and healthcare providers should balance the benefits of appropriate anesthesia in pregnant women, neonates, and young children who require procedures with the potential risks suggested by the nonclinical data. (See WARNINGS/ Pediatric Neurotoxicity, Pregnancy, and ANIMAL TOXICOLOGY AND/OR PHARMACOLOGY).

Geriatric Use

Clinical studies of BREVITAL did not include sufficient numbers of subjects aged 65 and over to determine whether they respond differently from younger subjects. Other reported clinical experience has not identified differences in responses between the elderly and younger patients. Elderly subjects may commonly have conditions in which methohexital should be used cautiously such as obstructive pulmonary disease, severe hypertension or hypotension, preexisting circulatory depression, myocardial disease, congestive heart failure, or severe anemia. Caution should be exercised in debilitated patients or in those with impaired function of respiratory, circulatory, renal, hepatic, or endocrine systems (see WARNINGS, PRECAUTIONS and ADVERSE REACTIONS). Barbiturates may influence the metabolism of other concomitantly used drugs that are commonly taken by the elderly, such as anticoagulants and corticosteroids. In general, dose selection for an elderly patient should be cautious, usually starting at the low end of the dosing range, reflecting the greater frequency of decreased hepatic, renal, or cardiac function, and of concomitant disease or other drug therapy (see PRECAUTIONS-Drug Interactions).

ADVERSE REACTIONS

Side effects associated with BREVITAL are extensions of pharmacologic effects and include:

Cardiovascular

Circulatory depression, thrombophlebitis, hypotension, tachycardia, peripheral vascular collapse, and convulsions in association with cardiorespiratory arrest

Respiratory

Respiratory depression (including apnea), cardiorespiratory arrest, laryngospasm, bronchospasm, hiccups, and dyspnea

Neurologic

Skeletal muscle hyperactivity (twitching), injury to nerves adjacent to injection site, and seizures

Psychiatric

Emergence delirium, restlessness, and anxiety may occur, especially in the presence of postoperative pain

Gastrointestinal

Nausea, emesis, abdominal pain, and liver function tests abnormal

Allergic

Erythema, pruritus, urticaria, and cases of anaphylaxis have been reported rarely

Other

Other adverse reactions include pain at injection site, salivation, headache, and rhinitis

For medical advice about adverse reactions contact your medical professional. To report SUSPECTED ADVERSE REACTIONS, contact Endo at 1-800-828-9393 or FDA at 1-800-FDA-1088 (1-800-332-1088) or www.fda.gov/medwatch/.

DRUG ABUSE AND DEPENDENCE

Controlled Substance—BREVITAL is a Schedule IV drug.

BREVITAL may be habit-forming.

OVERDOSAGE

Signs and Symptoms

The onset of toxicity following an overdose of intravenously administered methohexital will be within seconds of the infusion. If methohexital is administered rectally or is ingested, the onset of toxicity may be delayed. The manifestations of an ultrashort-acting barbiturate in overdose include central nervous system depression, respiratory depression, hypotension, loss of peripheral vascular resistance, and muscular hyperactivity ranging from twitching to convulsive-like movements. Other findings may include convulsions and allergic reactions. Following massive exposure to any barbiturate, pulmonary edema, circulatory collapse with loss of peripheral vascular tone, and cardiac arrest may occur.

Treatment

To obtain up-to-date information about the treatment of overdose, a good resource is your certified Regional Poison Control Center. Telephone numbers of certified poison control centers are listed in the Physicians’ Desk Reference (PDR). In managing overdosage, consider the possibility of multiple drug overdoses, interaction among drugs, and unusual drug kinetics in your patient.

Establish an airway and ensure oxygenation and ventilation. Resuscitative measures should be initiated promptly. For hypotension, intravenous fluids should be administered and the patient’s legs raised. If desirable increase in blood pressure is not obtained, vasopressor and/or inotropic drugs may be used as dictated by the clinical situation. For convulsions, diazepam intravenously and phenytoin may be required. If the seizures are refractory to diazepam and phenytoin, general anesthesia and paralysis with a neuromuscular blocking agent may be necessary.

Protect the patient’s airway and support ventilation and perfusion. Meticulously monitor and maintain, within acceptable limits, the patient’s vital signs, blood gases, serum electrolytes, etc. Absorption of drugs from the gastrointestinal tract may be decreased by giving activated charcoal, which, in many cases, is more effective than emesis or lavage; consider charcoal instead of or in addition to gastric emptying. Repeated doses of charcoal over time may hasten elimination of some drugs that have been absorbed. Safeguard the patient’s airway when employing gastric emptying or charcoal.

DOSAGE AND ADMINISTRATION

Facilities for assisting ventilation and administering oxygen are necessary adjuncts for all routes of administration of anesthesia. Since cardiorespiratory arrest may occur, patients should be observed carefully during and after use of BREVITAL. Age- and size- appropriate resuscitative equipment (i.e., intubation and cardioversion equipment, oxygen, suction, and a secure intravenous line) and personnel qualified in its use must be immediately available.

Preanesthetic medication is generally advisable. BREVITAL may be used with any of the recognized preanesthetic medications.

Preparation of Solution

FOLLOW DILUTION INSTRUCTIONS EXACTLY.

Freshly prepare solutions of BREVITAL and use promptly. Reconstituted solutions of BREVITAL are chemically stable at room temperature for 24 hours.

Diluents

ONLY USE BACTERIOSTATIC-FREE DILUENT – Recommended diluents are based on route of administration (see Dilution Instructions).

Incompatible diluents: Lactated Ringer’s Injection

Dilution Instructions

1% solutions (10 mg/mL) should be prepared for intermittent intravenous and rectal administration; 0.2% solutions (2 mg/mL) should be prepared for continuous intravenous drug administration; 5% solutions (50 mg/mL) should be prepared for intramuscular administration.

Contents of vials should be diluted as follows:

FOR INTERMITTENT INTRAVENOUS and RECTAL ADMINISTRATION

The preferred diluent for intermittent intravenous and rectal administration is Sterile Water for Injection. 5% Dextrose Injection, or 0.9% Sodium Chloride Injection are also acceptable diluents.

Strength | Amount of Diluent to Be Added to the Contents of the BREVITAL Vial | For 1% methohexital solution (10 mg/mL)
500 mg | 50 mL | no further dilution needed

FOR CONTINUOUS INTRAVENOUS ADMINISTRATION

For continuous drip anesthesia, prepare a 0.2% solution by adding 500 mg of BREVITAL Sodium to 250 mL of diluent. For this dilution, either 5% glucose solution or isotonic (0.9%) sodium chloride solution ONLY is recommended as the diluent instead of sterile water for injection in order to avoid extreme hypotonicity.

Strength | Amount of Diluent to Be Added to the Contents of the BREVITAL Vial | For 0.2% methohexital solution (2 mg/mL)
500 mg | 15 mL | add to 235 mL diluent for 250 mL total volume

FOR INTRAMUSCULAR ADMINISTRATION

The preferred diluent for intramuscular administration is Sterile Water for Injection. 0.9% Sodium Chloride Injection is also an acceptable diluent.

Strength | Amount of Diluent to Be Added to the Contents of the BREVITAL Vial | For 5% methohexital solution (50 mg/mL)
500 mg | 10 mL | no further dilution needed

Administration

Dosage is highly individualized; the drug should be administered only by those completely familiar with its quantitative differences from other barbiturate anesthetics.

Adults

BREVITAL is administered intravenously in a concentration of no higher than 1%. Higher concentrations markedly increase the incidence of muscular movements and irregularities in respiration and blood pressure.

Induction of anesthesia

For induction of anesthesia, a 1% solution is administered at a rate of about 1 mL/5 seconds. Gaseous anesthetics and/or skeletal muscle relaxants may be administered concomitantly. The dose required for induction may range from 50 to 120 mg or more but averages about 70 mg. The usual dosage in adults ranges from 1 to 1.5 mg/kg. The induction dose usually provides anesthesia for 5 to 7 minutes.

Maintenance of anesthesia may be accomplished by intermittent injections of the 1% solution or, more easily, by continuous intravenous drip of a 0.2% solution. Intermittent injections of about 20 to 40 mg (2 to 4 mL of a 1% solution) may be given as required, usually every 4 to 7 minutes. For continuous drip, the average rate of administration is about 3 mL of a 0.2% solution/minute (1 drop/second). The rate of flow must be individualized for each patient. For longer surgical procedures, gradual reduction in the rate of administration is recommended (see discussion of prolonged administration in WARNINGS). Other parenteral agents, usually narcotic analgesics, are ordinarily employed along with BREVITAL during longer procedures.

Pediatric Patients

BREVITAL is administered intramuscularly in a 5% concentration and administered rectally as a 1% solution.

Induction of anesthesia

For the induction of anesthesia by the intramuscular route of administration, the usual dose ranges from 6.6 to 10 mg/kg of the 5% concentration. For rectal administration, the usual dose for induction is 25 mg/kg using the 1% solution.

Parenteral drug products should be inspected visually for particulate matter and discoloration prior to administration, whenever solution and container permit.

Compatibility Information

Solutions of BREVITAL should not be mixed in the same syringe or administered simultaneously during intravenous infusion through the same needle with acid solutions, such as atropine sulfate, metocurine iodide, and succinylcholine chloride. Alteration of pH may cause free barbituric acid to be precipitated. Solubility of the soluble sodium salts of barbiturates, including BREVITAL, is maintained only at a relatively high (basic) pH.

Because of numerous requests from anesthesiologists for information regarding the chemical compatibility of these mixtures, the following chart contains information obtained from compatibility studies in which a 1% solution of BREVITAL was mixed with therapeutic amounts of agents whose solutions have a low (acid) pH.

Active Ingredient | Potency per mL | Volume Used | Immediate | 15 min | Physical Change 30 min | 1 h
BREVITAL | 10 mg | 10 mL |  |  | CONTROL
Atropine Sulfate | 1/150 gr | 1 mL | None | Haze
Atropine Sulfate | 1/100 gr | 1 mL | None | Ppt | Ppt
Succinylcholine chloride | 0.5 mg | 4 mL | None | None | Haze
Succinylcholine chloride | 1 mg | 4 mL | None | None | Haze
Metocurine Iodide | 0.5 mg | 4 mL | None | None | Ppt
Metocurine Iodide | 1 mg | 4 mL | None | None | Ppt
Scopolamine Hydrobromide | 1/120 gr | 1 mL | None | None | None | Haze
Tubocurarine chloride | 3 mg | 4 mL | None | Haze

HOW SUPPLIED

Store between 20° to 25°C (68° to 77°F). (See USP Controlled Room Temperature.)

BREVITAL® Vials*:

The 500 mg vials (with 30 mg anhydrous sodium carbonate) are available as follows:

NDC 42023-105-01 – Multi-Dose Vial – Pack of 1

*In crystalline form.

ANIMAL TOXICOLOGY AND/OR PHARMACOLOGY

Published studies in animals demonstrate that the use of anesthetic agents during the period of rapid brain growth or synaptogenesis results in widespread neuronal and oligodendrocyte cell loss in the developing brain and alterations in synaptic morphology and neurogenesis. Based on comparisons across species, the window of vulnerability to these changes is believed to correlate with exposures in the third trimester through the first several months of life, but may extend out to approximately 3 years of age in humans.

In primates, exposure to 3 hours of an anesthetic regimen that produced a light surgical plane of anesthesia did not increase neuronal cell loss, however, treatment regimens of 5 hours or longer increased neuronal cell loss. Data in rodents and in primates suggest that the neuronal and oligodendrocyte cell losses are associated with subtle but prolonged cognitive deficits in learning and memory. The clinical significance of these nonclinical findings is not known, and healthcare providers should balance the benefits of appropriate anesthesia in neonates and young children who require procedures against the potential risks suggested by the nonclinical data. (See WARNINGS/Pediatric Neurotoxicity, PRECAUTIONS/Pregnancy, Pediatric Use).

Rx only

Manufactured for:

Endo USA

Malvern, PA 19355

© 2024 Endo, Inc. or one of its affiliates.

R07/2024